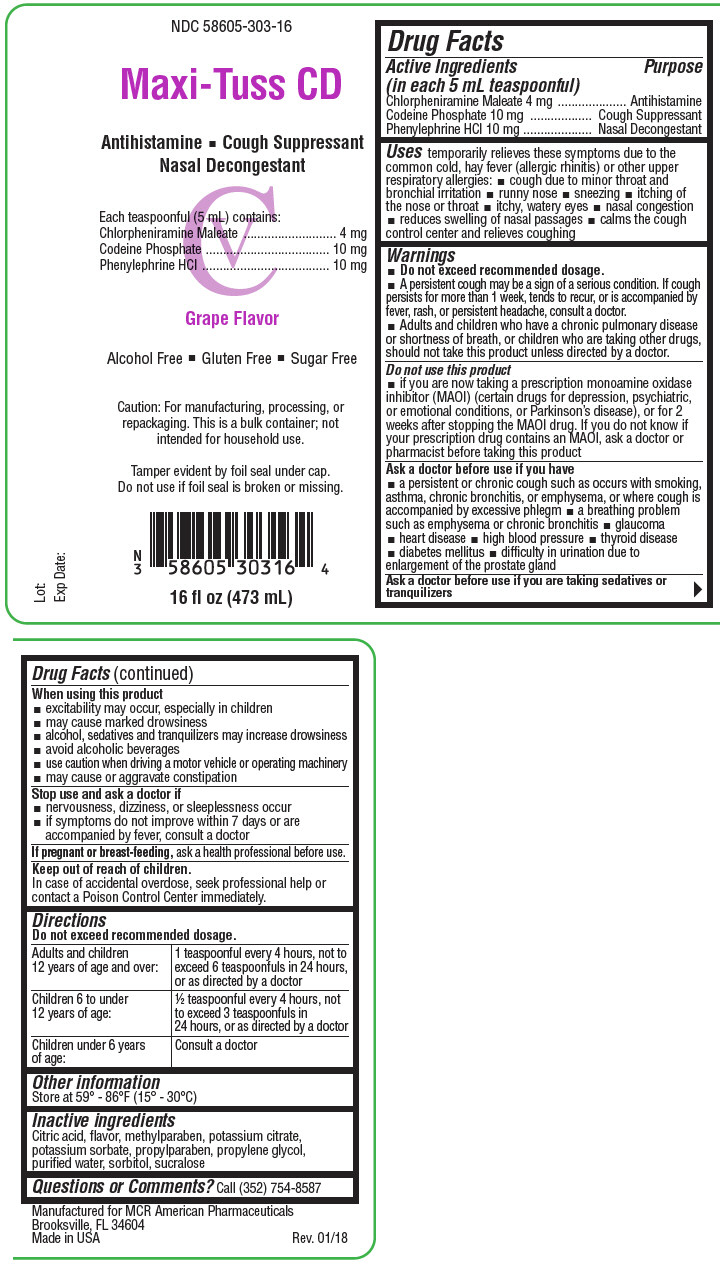 DRUG LABEL: Maxi-Tuss CD
NDC: 58605-303 | Form: LIQUID
Manufacturer: MCR American Pharmaceuticals, Inc.
Category: otc | Type: HUMAN OTC DRUG LABEL
Date: 20190821
DEA Schedule: CV

ACTIVE INGREDIENTS: CHLORPHENIRAMINE MALEATE 4 mg/5 mL; CODEINE PHOSPHATE 10 mg/5 mL; PHENYLEPHRINE HYDROCHLORIDE 10 mg/5 mL
INACTIVE INGREDIENTS: CITRIC ACID MONOHYDRATE; Methylparaben; Potassium Citrate; Potassium Sorbate; Propylparaben; Propylene Glycol; Water; Sorbitol; Sucralose

Maxi-Tuss CD

Drug Facts

ACTIVE INGREDIENT

Active Ingredients (in each 5 mL teaspoonful) | Purpose
Chlorpheniramine Maleate 4 mg | Antihistamine
Codeine Phosphate 10 mg | Cough Suppressant
Phenylephrine HCl 10 mg | Nasal Decongestant

Uses

temporarily relieves these symptoms due to the common cold, hay fever (allergic rhinitis) or other upper respiratory allergies:

- cough due to minor throat and bronchial irritation
- runny nose
- sneezing
- itching of the nose or throat
- itchy, watery eyes
- nasal congestion
- reduces swelling of nasal passages
- calms the cough control center and relieves coughing

Warnings

- Do not exceed recommended dosage.
- A persistent cough may be a sign of a serious condition. If cough persists for more than 1 week, tends to recur, or is accompanied by fever, rash, or persistent headache, consult a doctor.
- Adults and children who have a chronic pulmonary disease or shortness of breath, or children who are taking other drugs, should not take this product unless directed by a doctor.

Do not use this product

- if you are now taking a prescription monoamine oxidase inhibitor (MAOI) (certain drugs for depression, psychiatric, or emotional conditions, or Parkinson's disease), or for 2 weeks after stopping the MAOI drug. If you do not know if your prescription drug contains an MAOI, ask a doctor or pharmacist before taking this product

Ask a doctor before use if you have

- a persistent or chronic cough such as occurs with smoking, asthma, chronic bronchitis, or emphysema, or where cough is accompanied by excessive phlegm
- a breathing problem such as emphysema or chronic bronchitis
- glaucoma
- heart disease
- high blood pressure
- thyroid disease
- diabetes mellitus
- difficulty in urination due to enlargement of the prostate gland

Ask a doctor before use if you are taking sedatives or tranquilizers

When using this product

- excitability may occur, especially in children
- may cause marked drowsiness
- alcohol, sedatives and tranquilizers may increase drowsiness
- avoid alcoholic beverages
- use caution when driving a motor vehicle or operating machinery
- may cause or aggravate constipation

Stop use and ask a doctor if

- nervousness, dizziness, or sleeplessness occur
- if symptoms do not improve within 7 days or are accompanied by fever, consult a doctor

PREGNANCY OR BREAST FEEDING

If pregnant or breast-feeding, ask a health professional before use.

Keep out of reach of children.

In case of accidental overdose, seek professional help or contact a Poison Control Center immediately.

Directions

Do not exceed recommended dosage.

Adults and children 12 years of age and over: | 1 teaspoonful every 4 hours, not to exceed 6 teaspoonfuls in 24 hours, or as directed by a doctor
Children 6 to under 12 years of age: | ½ teaspoonful every 4 hours, not to exceed 3 teaspoonfuls in 24 hours, or as directed by a doctor
Children under 6 years of age: | Consult a doctor

Other information

Store at 59° - 86°F (15° - 30°C)

Inactive ingredients

Citric acid, flavor, methylparaben, potassium citrate, potassium sorbate, propylparaben, propylene glycol, purified water, sorbitol, sucralose

Questions or Comments?

Call (352) 754-8587

PRINCIPAL DISPLAY PANEL - 473 mL Bottle Label

NDC 58605-303-16

Maxi-Tuss CD

Antihistamine ◾ Cough Suppressant
Nasal Decongestant

CV

Each teaspoonful (5 mL) contains:
Chlorpheniramine Maleate 4 mg
Codeine Phosphate 10 mg
Phenylephrine HCl 10 mg

Grape Flavor

Alcohol Free ◾ Gluten Free ◾ Sugar Free

Caution: For manufacturing, processing, or
repackaging. This is a bulk container; not
intended for household use.

Tamper evident by foil seal under cap.
Do not use if foil seal is broken or missing.

Lot:
Exp Date:

16 fl oz (473 mL)